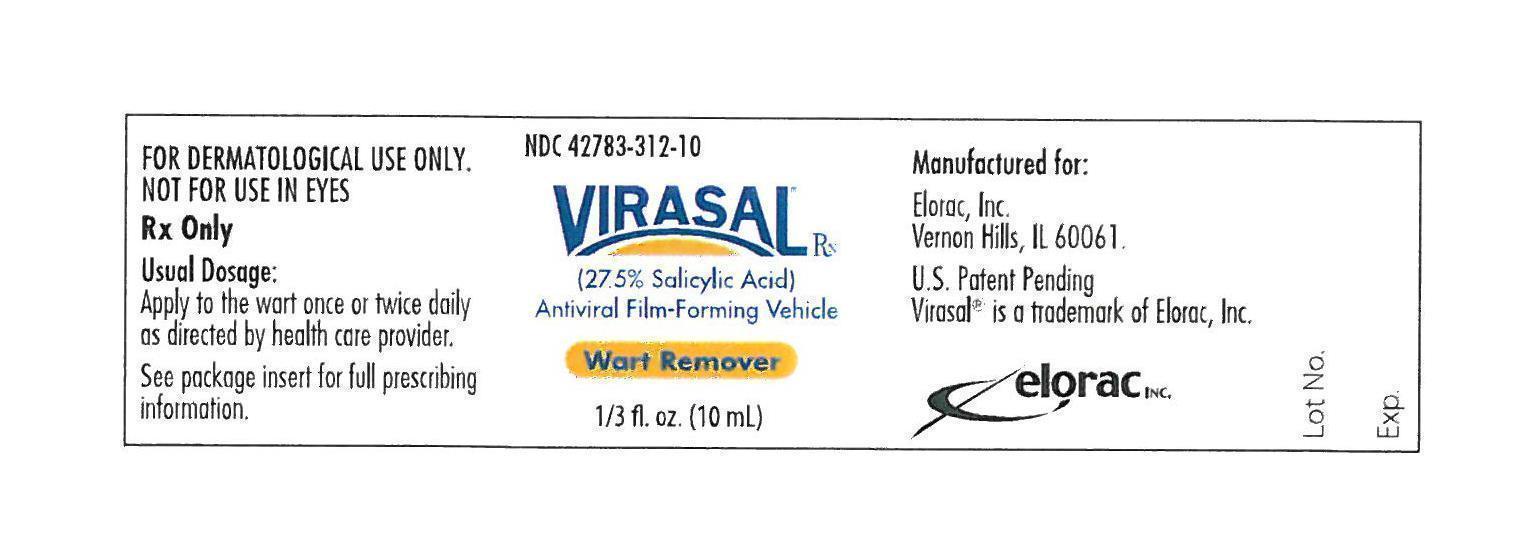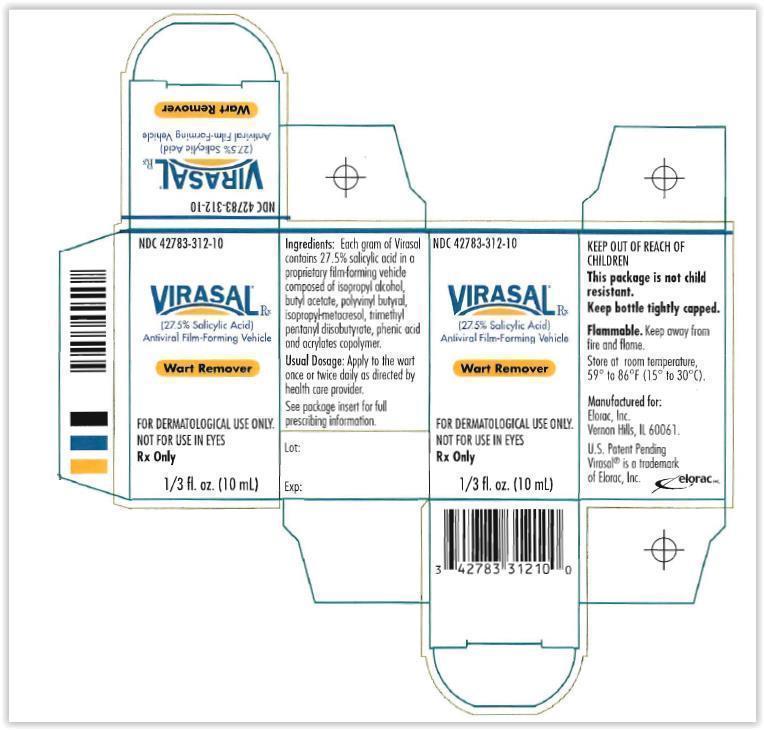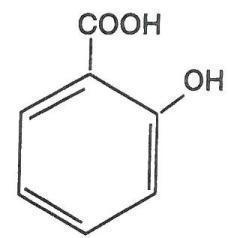 DRUG LABEL: Virasal
NDC: 42783-312 | Form: SOLUTION
Manufacturer: Elorac, Inc.
Category: prescription | Type: HUMAN PRESCRIPTION DRUG LABEL
Date: 20200115

ACTIVE INGREDIENTS: salicylic acid 275 mg/1 mL

Virasal (27.5% Salycylic Acid) Antiviral Film-Forming Vehicle - Package Insert Text:

Rx only

FOR TOPICAL USE ONLY.

NOT FOR OPHTHALMIC, ORAL OR INTRAVAGINAL USE.

DESCRIPTION

Virasal is a topical preparation containing 27.5% salicylic acid in a proprietary film-forming vehicle that comprises isopropyl alcohol, butyl acetate, polyvinyl butyral, isopropyl metacresol, trimethyl pentanyl diisobutyrate, phenic acid and acrylates copolymer. The pharmacologic activity of Virasal is generally attributed to the keratolytic activity of salicylic acid which is incorporated into a polyacrylic, film-forming virucidal vehicle designed to cover the wart without the need for a bandage. The structural formula of salicylic acid is:

CLINICAL PHARMACOLOGY

Although the exact mode of action for salicylic acid in the treatment of warts is unknown, its activity appears to be associated with its keratolytic action, which results in mechanical removal of epidermal cells infected with wart viruses.

The virucidal complex incorporated into Virasal’s proprietary vehicle is designed to help reduce risk of reinfection at the wart site, as well as prevent viral contamination of the product under normal usage.

INDICATIONS AND USAGE

Virasal is indicated for the topical treatment and removal of common warts and plantar warts.

CONTRAINDICATIONS

Patients with diabetes or impaired blood circulation should not use Virasal. Virasal also should not be used on moles, birthmarks, and unusual warts with hair growing from them, or warts on the face.

PRECAUTIONS

Virasal is for external use only. Do not permit Virasal to contact eyes or mucous membranes. If contact with eyes or mucous membranes occurs, immediately flush with water for 15 minutes. Virasal should not be allowed to contact normal skin surrounding wart, since localized irritation may occur. Treatment should be discontinued if excessive irritation occurs. Virasal is flammable. Keep away from fire or flame. Keep bottle tightly capped when not in use.

ADVERSE REACTIONS

A localized irritant reaction may occur if Virasal is applied to the normal skin surrounding the wart. Any irritation may normally be controlled by temporarily discontinuing use and by applying the medication only to the wart site when treatment is resumed.

DOSAGE AND ADMINISTRATION

Prior to applying Virasal, soak wart in warm water for five minutes. Remove any loosened tissue by gently rubbing with a brush, wash cloth, or emery board. Dry wart site thoroughly. Using the brush applicator supplied, apply Virasal twice to entire wart surface, allowing the first application to dry before applying the second. Continue treatment once or twice a day as directed by physician. Be careful not to apply to surrounding skin.

Clinically visible improvement will normally occur during the first or second week of therapy. Maximum resolution may be expected after four to six weeks of Virasal use.

HOW SUPPLIED

Virasal is supplied in 10ml amber bottles with a brush applicator (NDC 42783-312-10).

Store at controlled room temperature, 15° to 30°C (59° to 86°F).

Manufactured for:
Elorac, Inc.
Vernon Hills, IL 60061

U.S. Patent Pending

Revised 06/2011

221619

Virasal (27.5% Salycylic Acid) Antiviral Film-Forming Vehicle - Container Label Principal Display Panel Text:

NDC 42783-312-10

Virasal (27.5% Salycylic Acid) Antiviral Film-Forming Vehicle

Wart Remover

FOR TOPICAL USE ONLY
NOT FOR USE IN THE EYES

Rx only

1/3 fl. oz (10 mL)

Virasal (27.5% Salycylic Acid) Antiviral Film-Forming Vehicle - Carton Label Principal Display Panel Text:

NDC 42783-312-10

Virasal (27.5% Salycylic Acid) Antiviral Film-Forming Vehicle

Wart Remover

FOR DERMATOLOGICAL USE ONLY
NOT FOR USE IN THE EYES

Rx only

1/3 fl. oz (10 mL)